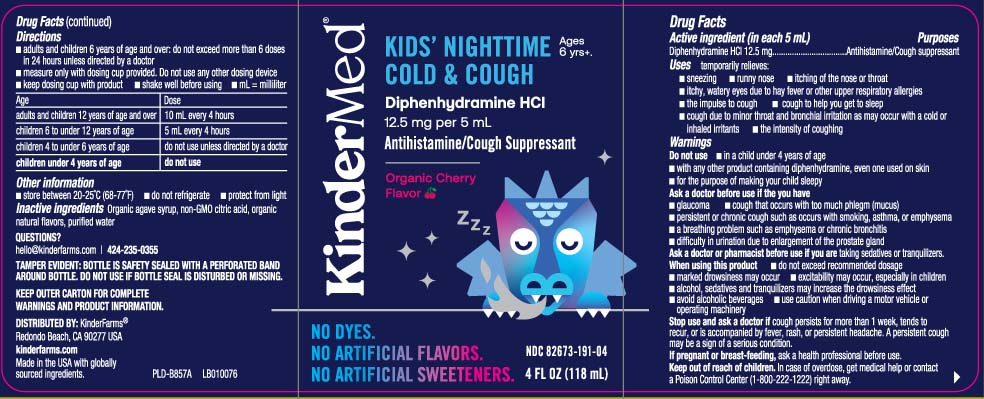 DRUG LABEL: Nighttime Cold and Cough
NDC: 82673-191 | Form: LIQUID
Manufacturer: KinderFarms, LLC
Category: otc | Type: HUMAN OTC DRUG LABEL
Date: 20241001

ACTIVE INGREDIENTS: DIPHENHYDRAMINE HYDROCHLORIDE 12.5 mg/5 mL
INACTIVE INGREDIENTS: AGAVE TEQUILANA JUICE; CITRIC ACID MONOHYDRATE; WATER

Drug Facts

Active ingredients (in each 5 mL)

Diphenhydramine HCl 12.5 mg

Purposes

Antihistamine/

Cough suppressant

Uses

temporarily relieves:

- sneezing
- runny nose
- itchy nose or throat
- itchy, watery eyes due to hay fever or other upper respiratory allergies
- the impulse to cough
- cough to help you get to sleep
- cough due to minor throat and bronchial irritation as may occur with a cold or inhaled irritant
- the intensity of coughing

Warnings

Do not use

- in a child under 4 years of age
- with any other product containing diphenhydramine, even one used on skin
- for the purpose of making your child sleepy

Ask a doctor before use if the chld has

- glaucoma
- cough that occurs with too much phlegm (mucus)
- persistent or chronic cough such as occurs with smoking, asthma, or emphysema
- diabetes
- a breathing problem such as emphysema or chronic bronchitis
- difficulty in urination due to enlargement of the prostate gland

Ask a doctor or pharmacist before use if the child is

taking sedatives or tranquilizers

When using this product

- do not exceed recommended dosage
- marked drowsiness may occur
- excitability may occur, especially in children
- alcohol, sedatives and tranquilizers may increase drowsiness effect
- avoid alcoholic beverages
- use caution when driving a motor vehicle or operating machinery

Stop use and ask a doctor if

- cough persists for more than 1 week, tends to recur, or is accompanied by fever, rash, or persistent headache. A persistent cough may be a sign of a serious condition.

If pregnant or breat-feeding,

ask a health professional before use.

Keep out of reach of children.

In case of overdose, get medical help or contact a Poison Control Center (1-800-222-1222) right away.

Directions

- adults and children 6 years and over: do not exceed more than 6 doses in any 24-hours unless directed by a doctor
- measure only with dosing cup provided. Do not use any other dosing device
- keep dosing cup with product
- shake well before using
- mL= milliliter

Age | Dose
adults and children 12 years of age and over | 10 mL every 4 hours
children 6 to under 12 years of age | 5 mL every 4 hours
children 4 to under 6 years of age | do not use unless directed by a doctor
children under 4 years of age | do not use

Other information

- store between 20-25º (68-77ºF).
- Do not refrigerate
- protect from light

Inactive ingredients

Organic agave syrup, non-GMO citric acid, organic natural flavor, purified water

QUESTIONS?

Call 424-235-0355

Principal Display Panel

KIDS' Ages 6 yrs+.

NIGHTTIME

COLD & COUGH

Diphenhydramine HCl 12.5 mg per 5 mL

Antihistamine/Cough Suppressant

Organic Cherry Flavor

DOSING CUP INCLUDED

FL OZ (mL)

TAMPER EVIDENT: BOTTLE IS SAFETY SEALED WITH A PERFORATED BAND AROUND BOTTLE. DO NOT USE IF BOTTLE SEAL IS DISTURBED OR MISSING.

KEEP OUTER CARTON FOR COMPLETE WARNINGS AND PRODUCT INFORMATION.

DISTRIBUTED BY: KinderFarms®

Redondo Beach, CA 90277 USA

Package Label

KINDERMED Kids Nighttime Cold & Cough Organic Cherry Flavor